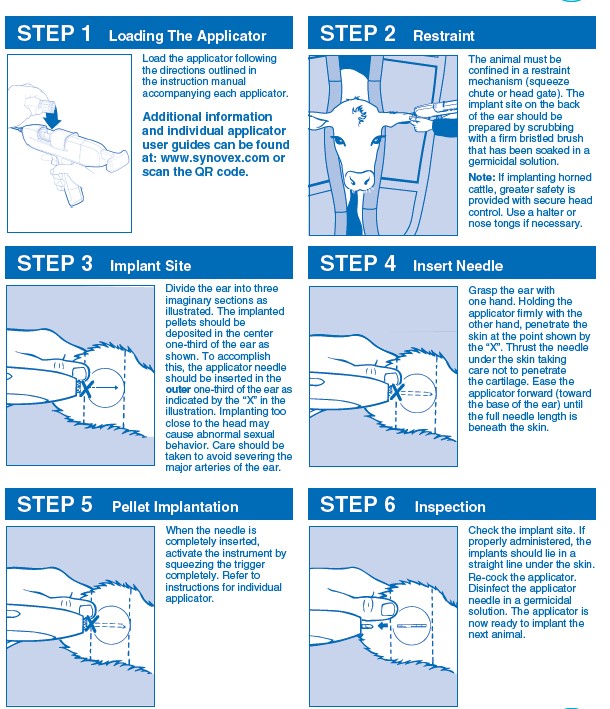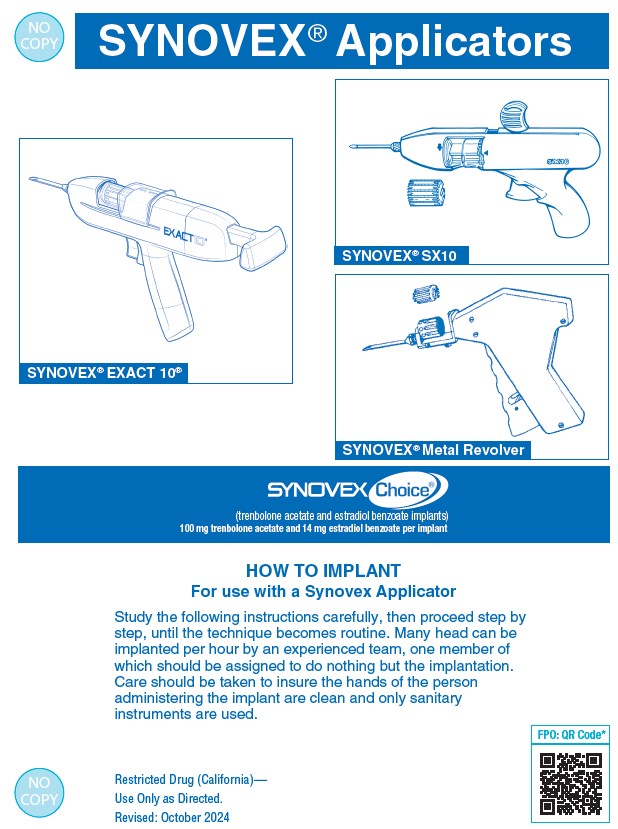 DRUG LABEL: Synovex Choice
NDC: 54771-3908 | Form: IMPLANT
Manufacturer: Zoetis Inc.
Category: animal | Type: OTC ANIMAL DRUG LABEL
Date: 20250221

ACTIVE INGREDIENTS: TRENBOLONE ACETATE 100 mg/1 1; ESTRADIOL BENZOATE 14 mg/1 1

SYNOVEX Choice®

SUBCUTANEOUS IMPLANTS FOR GROWING BEEF STEERS AND HEIFERS ON PASTURE, IN A DRY LOT AND FED IN CONFINEMENT FOR SLAUGHTER
SYNOVEX Choice®
(trenbolone acetate and estradiol benzoate implants)
100 mg trenbolone acetate and 14 mg estradiol benzoate per implant

DESCRIPTION

SYNOVEX Choice® (trenbolone acetate and estradiol benzoate implants) is a growth promoting implant containing 100 mg of trenbolone acetate and 14 mg of estradiol benzoate per implant. Each implant consists of 4 pellets. Ten implants are provided in each cartridge.
NOTE: Administration of a single SYNOVEX Choice® implant or its use in a reimplantation program with a SYNOVEX Choice®, SYNOVEX Plus®, or SYNOVEX® ONE Feedlot implant may result in decreased marbling scores when compared to non-implanted steers and heifers.

WITHDRAWAL PERIODS AND RESIDUE WARNINGS

No withdrawal period is required when used according to labeling.
Do not use in beef calves less than 2 months of age, dairy calves, and veal calves. A withdrawal period has not been established for this product in pre-ruminating calves.
Do not use in dairy cows or in animals intended for subsequent breeding. Use in these cattle may cause drug residues in milk and/or in calves born to these cows.
Implant pellets subcutaneously in ear only. Any other location is a violation of Federal law. Do not attempt salvage of implanted site for human or animal food.

USER SAFETY WARNINGS

Not for use in humans. Keep out of reach of children.

ANIMAL SAFETY WARNINGS

Bulling has occasionally been reported in implanted steers and heifers. Vaginal and rectal prolapse, udder development, ventral edema and elevated tailheads have occasionally been reported in heifers administered SYNOVEX Choice® implants.

DIRECTIONS

Administer one SYNOVEX Choice® implant (four pellets), containing 100 mg of trenbolone acetate and 14 mg of estradiol benzoate, to each steer or heifer by subcutaneous implantation in the middle-third of the ear. If using in a reimplantation program, reimplant steers or heifers 60 to 120 days later with a SYNOVEX Choice®, SYNOVEX Plus®, or SYNOVEX® ONE Feedlot implant.
Use only a SYNOVEX applicator. Approved implantation technique is fully described in the fold-out carton section. Never sacrifice careful, clean technique for speed of implantation.

STORAGE

Store unopened product at controlled room temperature 20°-25°C (68°-77°F) with excursions between 15°-30°C (59°-86°F). Avoid excessive heat and humidity. Use product before the expiration date on the label.
Once the pouch is opened, unused product may be stored in the end-folded pouch (away from light) for up to six months under refrigerated conditions 2°-8°C (36°-47°F) or at room temperature 20°-25°C (68°-77°F) with excursions between 15°-30°C (59°-86°F) for up to one month.

DISPOSAL

SYNOVEX Choice® waste materials should be disposed of according to prescribed Federal, State, and Local guidelines.

INDICATIONS FOR USE

- For increased rate of weight gain in growing beef steers and heifers on pasture (stocker, feeder, and slaughter).
- For increased rate of weight gain in growing beef steers and heifers in a dry lot.
- For increased rate of weight gain in growing beef steers fed in confinement for slaughter and for increased rate of weight gain and improved feed efficiency in growing beef heifers fed in confinement for slaughter.
- For increased rate of weight gain for up to 200 days in growing beef steers and heifers fed in confinement for slaughter in a reimplantation program where SYNOVEX Choice® is the first implant and a SYNOVEX Choice®, SYNOVEX Plus®, or SYNOVEX® ONE Feedlot implant is administered 60 to 120 days later.
- Other than as described on the labeling, this implant is not approved for repeated implantation (reimplantation) with any other cattle ear implant in growing beef steers and heifers fed in confinement for slaughter, on pasture, or in a dry lot as safety and effectiveness have not been evaluated.

Do not use in beef calves less than 2 months of age, dairy calves, and veal calves because effectiveness and safety have not been established.

Do not use in animals intended for subsequent breeding, or in dairy cows.

QUESTIONS/COMMENTS?

For a copy of the Safety Data Sheet or to report side effects, contact Zoetis Inc. at 1-888-963-8471. For additional information about reporting side effects for animal drugs, contact FDA at 1-888-FDA-VETS or http://www.fda.gov/reportanimalae.

SYNOVEX Plus® (trenbolone acetate and estradiol benzoate implants) and SYNOVEX® ONE Feedlot (trenbolone acetate and estradiol extended-release implants) are owned by Zoetis.
Manufactured By A Non-Sterilizing Process
Restricted Drug (California)—Use Only As Directed.

IMPORTANT

Read ALL sides of carton

NET CONTENTS: 10 CARTRIDGES
Each Cartridge Contains 10 implants (100 implants total)

Approved by FDA under NADA # 141-043
zoetis
Distributed by:
Zoetis Inc.
Kalamazoo, MI 49007
40049036

PRINCIPAL DISPLAY PANEL - 10 Cartridge Implant Carton

40049036